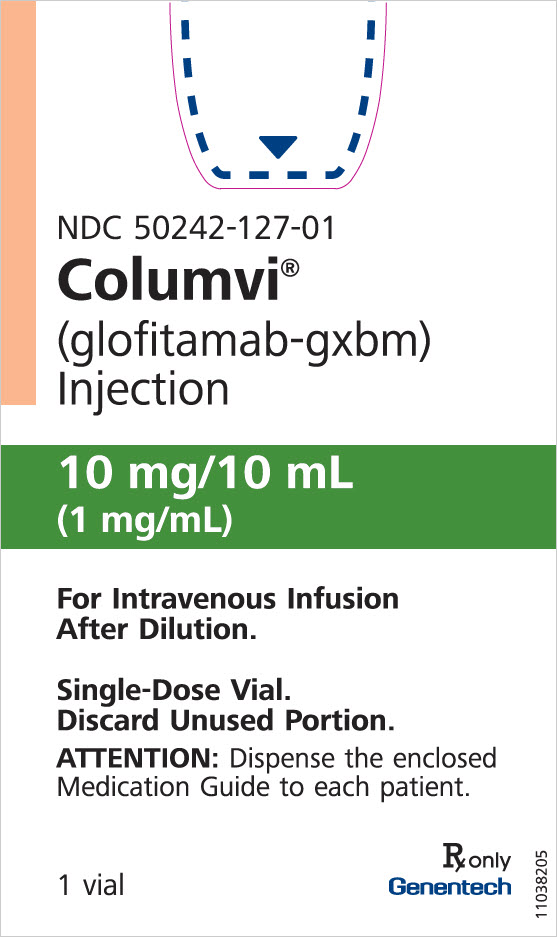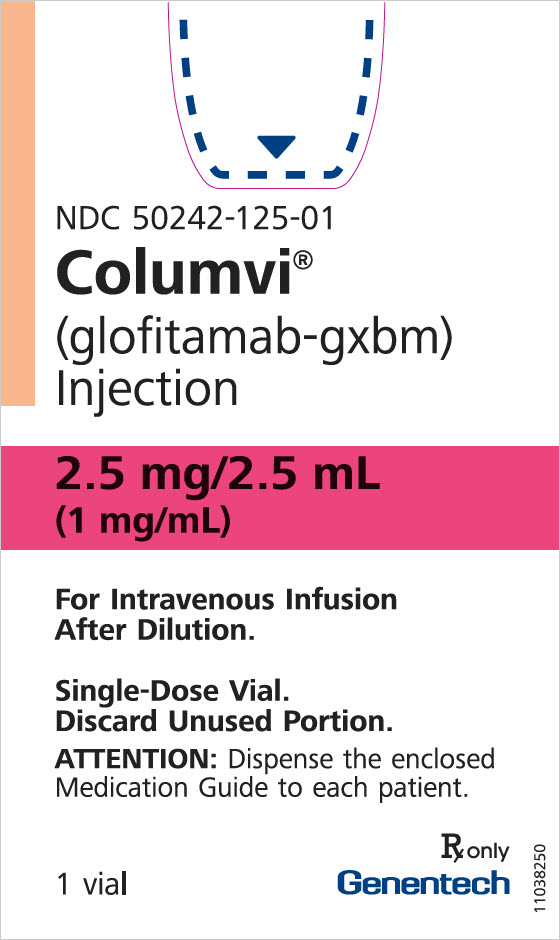 DRUG LABEL: Columvi
NDC: 50242-127 | Form: CONCENTRATE
Manufacturer: Genentech, Inc.
Category: prescription | Type: HUMAN PRESCRIPTION DRUG LABEL
Date: 20251103

ACTIVE INGREDIENTS: GLOFITAMAB 10 mg/10 mL
INACTIVE INGREDIENTS: HISTIDINE 6.3 mg/10 mL; HISTIDINE HYDROCHLORIDE MONOHYDRATE 33.4 mg/10 mL; METHIONINE 14.9 mg/10 mL; SUCROSE 821.5 mg/10 mL; POLYSORBATE 20 5 mg/10 mL

HIGHLIGHTS OF PRESCRIBING INFORMATION

These highlights do not include all the information needed to use COLUMVI® safely and effectively. See full prescribing information for COLUMVI.
COLUMVI (glofitamab-gxbm) injection, for intravenous use
Initial U.S. Approval: 2023

WARNING: CYTOKINE RELEASE SYNDROME

See full prescribing information for complete boxed warning

Cytokine Release Syndrome (CRS), including serious or fatal reactions, can occur in patients receiving COLUMVI. Premedicate before each dose, and initiate treatment with the COLUMVI step-up dosing schedule to reduce the risk of CRS. Withhold COLUMVI until CRS resolves or permanently discontinue based on severity. (2.1, 2.2, 2.3, 2.4, 5.1)

RECENT MAJOR CHANGES

Dosage and Administration (2.1, 2.3, 2.5, 2.6, 2.7) | 10/2025

1 INDICATIONS AND USAGE

COLUMVI is a bispecific CD20-directed CD3 T-cell engager indicated for the treatment of adult patients with relapsed or refractory diffuse large B-cell lymphoma, not otherwise specified (DLBCL, NOS) or large B-cell lymphoma (LBCL) arising from follicular lymphoma, after two or more lines of systemic therapy.

This indication is approved under accelerated approval based on response rate and durability of response. Continued approval for this indication may be contingent upon verification and description of clinical benefit in a confirmatory trial(s). (1)

2 DOSAGE AND ADMINISTRATION

- Pretreat with a single 1,000 mg dose of obinutuzumab intravenously 7 days before initiation of COLUMVI (Cycle 1 Day 1). (2.2)
- Administer premedications as recommended. (2.3)
- Administer only as an intravenous infusion. (2.1)
- Recommended dosage (2.2):
  Treatment Cycle [Cycle = 21 days] | Day | Dose of COLUMVI
   | Day 1 | Obinutuzumab 1,000 mg
  Cycle 1 | Day 8 | Step-up dose 1 | 2.5 mg
   | Day 15 | Step-up dose 2 | 10 mg
  Cycle 2 to 12 | Day 1 | 30 mg
- Administer in a facility equipped to monitor and manage CRS. (2.1, 2.2)
- Patients should be hospitalized for the 2.5 mg step-up dose and for subsequent infusions as recommended. (2.1, 2.2)
- See Full Prescribing Information for instructions on preparation and administration. (2.5, 2.6, 2.7)

3 DOSAGE FORMS AND STRENGTHS

Injection:

- 2.5 mg/2.5 mL (1 mg/mL) in a single-dose vial. (3)
- 10 mg/10 mL (1 mg/mL) in a single-dose vial. (3)

4 CONTRAINDICATIONS

None. (4)

5 WARNINGS AND PRECAUTIONS

- Neurologic Toxicity: Can cause serious neurologic toxicity, including Immune Effector Cell-Associated Neurotoxicity Syndrome (ICANS). Monitor for neurologic toxicity; withhold or permanently discontinue based on severity. (5.2)
- Serious Infections: Can cause serious or fatal infections. Monitor patients for signs and symptoms of infection and treat appropriately. (5.3)
- Tumor Flare: Can cause serious tumor flare reactions. Monitor patients at risk for complications of tumor flare. (5.4)
- Embryo-Fetal Toxicity: May cause fetal harm. Advise females of reproductive potential of the potential risk to the fetus and to use effective contraception. (5.5, 8.1, 8.3)

6 ADVERSE REACTIONS

The most common (≥ 20%) adverse reactions, excluding laboratory abnormalities, are cytokine release syndrome, musculoskeletal pain, rash, and fatigue. The most common (≥ 20%) Grade 3 to 4 laboratory abnormalities are lymphocyte count decreased, phosphate decreased, neutrophil count decreased, uric acid increased, and fibrinogen decreased. (6.1)

To report SUSPECTED ADVERSE REACTIONS, contact Genentech at 1-888-835-2555 or FDA at 1-800-FDA-1088 or www.fda.gov/medwatch.

8 USE IN SPECIFIC POPULATIONS

Lactation: Advise not to breastfeed. (8.2)

FULL PRESCRIBING INFORMATION

WARNING: CYTOKINE RELEASE SYNDROME

Cytokine Release Syndrome (CRS), including serious or fatal reactions, can occur in patients receiving COLUMVI. Premedicate before each dose, and initiate treatment with the COLUMVI step-up dosing schedule to reduce the risk of CRS. Withhold COLUMVI until CRS resolves or permanently discontinue based on severity [see Dosage and Administration (2.1, 2.2, 2.3, and 2.4) and Warnings and Precautions (5.1)].

1 INDICATIONS AND USAGE

COLUMVI is indicated for the treatment of adult patients with relapsed or refractory diffuse large B-cell lymphoma, not otherwise specified (DLBCL, NOS) or large B-cell lymphoma (LBCL) arising from follicular lymphoma, after two or more lines of systemic therapy.

This indication is approved under accelerated approval based on response rate and durability of response [see Clinical Studies (14.1)]. Continued approval for this indication may be contingent upon verification and description of clinical benefit in a confirmatory trial(s).

2 DOSAGE AND ADMINISTRATION

2.1 Important Dosing Information

- Administer only as an intravenous infusion through a dedicated infusion line that includes a sterile 0.2-micron in-line filter.
- Administer COLUMVI diluted solution via intravenous bag infusion. The 2.5 mg dose may alternatively be administered via intravenous syringe infusion [see Dosage and Administration (2.5, 2.6, 2.7)].
- COLUMVI should only be administered by a healthcare professional with immediate access to appropriate medical support, including supportive medications to manage severe CRS [see Dosage and Administration (2.4)].
- Ensure adequate hydration before administering COLUMVI.
- Premedicate before each dose [see Dosage and Administration (2.3)].
- Following pretreatment with obinutuzumab, administer COLUMVI according to the step-up dosing schedule in Table 1 with appropriate premedication, including dexamethasone, to reduce the incidence and severity of CRS [see Dosage and Administration (2.3)].
- Due to the risk of CRS, patients should be hospitalized during and for 24 hours after completion of infusion of step-up dose 1 (2.5 mg on Cycle 1 Day 8) [see Dosage and Administration (2.2) and Warnings and Precautions (5.1)].
- Patients who experienced any grade CRS during step-up dose 1 should be hospitalized during and for 24 hours after completion of step-up dose 2 (10 mg on Cycle 1 Day 15). CRS with step-up dose 2 can occur in patients who did not experience CRS with step-up dose 1 [see Dosage and Administration (2.2) and Warnings and Precautions (5.1)].
- For subsequent doses, patients who experienced Grade ≥ 2 CRS with their previous infusion should be hospitalized during and for 24 hours after the completion of the next COLUMVI infusion.

2.2 Recommended Dosage

Pretreatment with Obinutuzumab

Pretreat all patients with a single 1,000 mg dose of obinutuzumab administered as an intravenous infusion on Cycle 1 Day 1, 7 days prior to initiation of COLUMVI (see Table 1) to deplete the circulating and lymphoid tissue B cells.

Obinutuzumab should be administered as an intravenous infusion at 50 mg/hour. The rate of infusion can be escalated in 50 mg/hour increments every 30 minutes to a maximum of 400 mg/hour. Refer to the obinutuzumab prescribing information for complete dosing information.

COLUMVI Step-up Dose Schedule

COLUMVI dosing begins with a step-up dose schedule. Following completion of pretreatment with obinutuzumab on Cycle 1 Day 1, administer COLUMVI as an intravenous infusion according to the step-up dose schedule in Table 1. Administer premedications for each dose of COLUMVI as described in Table 3 [see Dosage and Administration (2.3)].

Table 1: COLUMVI Dosing Schedule (21-Day Treatment Cycles)
Treatment cycle | Day | Dose of COLUMVI |  | Duration of infusion
Cycle 1 | Day 1 | Obinutuzumab [Refer to "Pretreatment with obinutuzumab" described above.]
Cycle 1 | Day 8 | Step-up dose 1 | 2.5 mg | 4 hours [For patients who experience CRS with their previous dose of COLUMVI, the time of infusion may be extended up to 8 hours.]
 | Day 15 | Step-up dose 2 | 10 mg | 4 hours [For patients who experience CRS with their previous dose of COLUMVI, the time of infusion may be extended up to 8 hours.]
Cycle 2 | Day 1 | 30 mg |  | 4 hours
Cycle 3 to 12 | Day 1 | 30 mg |  | 2 hours [If the patient experienced CRS with the previous dose, the duration of infusion should be maintained at 4 hours.]

Continue COLUMVI for a maximum of 12 cycles (inclusive of Cycle 1 step-up dosing) or until disease progression or unacceptable toxicity, whichever occurs first.

Monitoring for Cytokine Release Syndrome [see Warnings and Precautions (5.1)]

- Administer the COLUMVI infusions intravenously in a healthcare setting with immediate access to medical support to manage CRS, including severe CRS.
- For the first COLUMVI step-up dose (2.5 mg on Cycle 1 Day 8), patients should be hospitalized during and for 24 hours after completion of the COLUMVI infusion.
- Patients who experienced any grade CRS during step-up dose 1 should be hospitalized during and for 24 hours after completion of step-up dose 2 (10 mg on Cycle 1 Day 15). CRS with step-up dose 2 can occur in patients who did not experience CRS with step-up dose 1.
- For subsequent infusions (30 mg on Day 1 of Cycle 2 or subsequent cycles), patients who experienced Grade ≥ 2 CRS with their previous infusion should be hospitalized during and for 24 hours after completion of the next COLUMVI infusion.
- For monitoring after delayed or missed doses of COLUMVI, follow the recommendations in Table 2.

Delayed or Missed Doses

If a dose of COLUMVI is delayed, restart therapy based on the recommendations made in Table 2, then resume the treatment schedule accordingly.

For repeat of the 2.5 mg dose patients should be hospitalized during and for 24 hours after completion of the COLUMVI infusion. For the repeat of the 10 mg dose, patients should be hospitalized during and for 24 hours after completion of the COLUMVI infusion if any grade CRS occurred during the most recent 2.5 mg dose.

Table 2: Recommendations for Restarting COLUMVI After Dose Delay
Last Dose Administered | Time Since Last Dose Administered | Action for Next Dose(s) [Administer premedication as per Table 3 for all patients.]
Obinutuzumab pretreatment (Cycle 1 Day 1) | ≤ 2 weeks | - Administer COLUMVI 2.5 mg (Cycle 1 Day 8) [Patients should be hospitalized during and for 24 hours after completing infusion of the 2.5 mg dose.] , then resume the planned treatment schedule.
Obinutuzumab pretreatment (Cycle 1 Day 1) | > 2 weeks | - Repeat obinutuzumab 1,000 mg pretreatment (Cycle 1 Day 1). - Then administer COLUMVI 2.5 mg (Cycle 1 Day 8) and resume the planned treatment schedule.
COLUMVI 2.5 mg (Cycle 1 Day 8) | ≤ 2 weeks | - Administer COLUMVI 10 mg (Cycle 1 Day 15) [Patients should be hospitalized during and for 24 hours after completing infusion of the 10 mg dose if CRS occurred during the most recent 2.5 mg dose.] , then resume the planned treatment schedule.
 | > 2 to ≤ 4 weeks | - Repeat COLUMVI 2.5 mg (Cycle 1 Day 8). - Then administer COLUMVI 10 mg (Cycle 1 Day 15) and resume the planned treatment schedule.
 | > 4 weeks | - Repeat obinutuzumab 1,000 mg pretreatment (Cycle 1 Day 1) and COLUMVI 2.5 mg (Cycle 1 Day 8). - Then administer COLUMVI 10 mg (Cycle 1 Day 15) and resume the planned treatment schedule.
COLUMVI 10 mg (Cycle 1 Day 15) | ≤ 2 weeks | - Administer COLUMVI 30 mg (Cycle 2 Day 1), then resume the planned treatment schedule.
 | > 2 to ≤ 6 weeks | - Repeat COLUMVI 10 mg (Cycle 1 Day 15). - Then administer COLUMVI 30 mg (Cycle 2 Day 1) and resume the planned treatment schedule.
 | > 6 weeks | - Repeat obinutuzumab 1,000 mg pretreatment (Cycle 1 Day 1), COLUMVI 2.5 mg (Cycle 1 Day 8), and COLUMVI 10 mg (Cycle 1 Day 15). - Then administer COLUMVI 30 mg (Cycle 2 Day 1) and resume the planned treatment schedule.
COLUMVI 30 mg (Cycle 2 onwards) | ≤ 6 weeks | - Administer COLUMVI 30 mg, then resume the planned treatment schedule.
 | > 6 weeks | - Repeat the Cycle 1 regimen described in Table 1: obinutuzumab 1,000 mg pretreatment (Day 1), COLUMVI 2.5 mg (Day 8), and COLUMVI 10 mg (Day 15). - Then administer COLUMVI 30 mg (Day 1 of next cycle) and resume the planned treatment schedule.

2.3 Recommended Premedication and Prophylactic Medications

Premedication

Administer the following premedications to reduce the risk of CRS and infusion-related reactions [see Warnings and Precautions (5.1)].

Table 3: Premedications to be Administered for COLUMVI Infusion
Day of Treatment Cycle | Patients requiring premedication | Premedication | Administration
Cycle 1, Day 8 and Day 15; Cycle 2; Cycle 3 |  | Dexamethasone 20 mg intravenously [If dexamethasone is not available, administer prednisone 100 mg, prednisolone 100 mg, or methylprednisolone 80 mg intravenously.] | Completed at least 1 hour prior to COLUMVI infusion.
Cycle 1, Day 8 and Day 15; Cycle 2; Cycle 3 | All patients | Acetaminophen 500 mg to 1,000 mg orally | At least 30 minutes before COLUMVI infusion.
Cycle 1, Day 8 and Day 15; Cycle 2; Cycle 3 |  | Antihistamine (diphenhydramine 50 mg orally or intravenously or equivalent) | Completed at least 30 minutes before COLUMVI infusion.
All subsequent infusions | All patients | Acetaminophen 500 mg to 1,000 mg orally | At least 30 minutes before COLUMVI infusion.
All subsequent infusions | All patients | Antihistamine (diphenhydramine 50 mg orally or intravenously or equivalent) | Completed at least 30 minutes before COLUMVI infusion.
All subsequent infusions | Patients who experienced any grade CRS with the previous dose | Dexamethasone 20 mg intravenously | Completed at least 1 hour prior to COLUMVI infusion.

Tumor Lysis Syndrome Prophylaxis

Before starting COLUMVI, administer anti-hyperuricemics to patients at risk of tumor lysis syndrome, ensure adequate hydration status, and monitor as appropriate [see Adverse Reactions (6.1)].

Infection Prophylaxis

Before starting COLUMVI, consider initiation of antiviral prophylaxis to prevent herpes virus reactivation. Consider prophylaxis for cytomegalovirus infection, pneumocystis jirovecii pneumonia (PJP), and other opportunistic infections in patients at increased risk [see Warnings and Precautions (5.3)].

2.4 Dosage Modifications for Adverse Reactions

No dosage reduction for COLUMVI is recommended.

Cytokine Release Syndrome

Identify CRS based on clinical presentation [see Warnings and Precautions (5.1)]. Evaluate for and treat other causes of fever, hypoxia, and hypotension.

If CRS is suspected, withhold COLUMVI and manage according to the recommendations in Table 4 and current practice guidelines. Administer supportive care for CRS, which may include intensive care for severe or life-threatening cases.

Table 4: Recommendations for Management of Cytokine Release Syndrome
Grade [American Society for Transplantation and Cellular Therapy (ASTCT) 2019 consensus grading criteria.] | Presenting Symptoms | Actions
Grade 1 | Temperature ≥ 100.4°F (38°C) [Premedication may mask fever. Therefore, if clinical presentation is consistent with CRS, follow these management guidelines.] | - Withhold COLUMVI and manage per current practice guidelines. - If symptoms resolve, restart infusion at a slower rate. [Duration of infusion may be extended up to 8 hours, as appropriate for that cycle (see Table 1).] - Ensure CRS symptoms are resolved for at least 72 hours before next dose. [Refer to Table 2 for information on restarting COLUMVI after dose delays [see Dosage and Administration (2.2)].] - Consider slower infusion rate for next dose.
Grade 2 | Temperature ≥ 100.4°F (38°C) with: Hypotension not requiring vasopressors and/or Hypoxia requiring low-flow oxygen [Low-flow oxygen defined as oxygen delivered at < 6 L/minute, high-flow oxygen defined as oxygen delivered at ≥ 6 L/minute.] by nasal cannula or blow-by | - Withhold COLUMVI and manage per current practice guidelines. - If symptoms resolve, restart infusion at a slower rate. - Ensure CRS symptoms are resolved for at least 72 hours before next dose. - For the next dose, consider a slower infusion rate, monitor more frequently, and consider hospitalization. - For recurrent Grade 2 CRS, manage per Grade 3 CRS.
Grade 3 | Temperature ≥ 100.4°F (38°C) with: Hypotension requiring vasopressor (with or without vasopressin) and/or Hypoxia requiring high-flow oxygen by nasal cannula, face mask, non-rebreather mask, or Venturi mask | - Withhold COLUMVI and manage per current practice guidelines, which may include intensive care. - Ensure CRS symptoms are resolved for at least 72 hours before next dose. - Hospitalize for the next dose, monitor more frequently, and consider a slower infusion rate. - For recurrent Grade 3 CRS, permanently discontinue COLUMVI.
Grade 4 | Temperature ≥ 100.4°F (38°C) with: Hypotension requiring multiple vasopressors (excluding vasopressin) and/or Hypoxia requiring oxygen by positive pressure (e.g., CPAP, BiPAP, intubation, and mechanical ventilation) | - Permanently discontinue COLUMVI and manage per current practice guidelines, which may include intensive care.

Neurologic Toxicity, Including ICANS

Management recommendations for neurologic toxicity, including ICANS, is summarized in Table 5. At the first sign of neurologic toxicity, including ICANS, consider neurology evaluation and withholding COLUMVI based on the type and severity of neurotoxicity. Rule out other causes of neurologic symptoms. Provide supportive therapy, which may include intensive care.

Table 5: Recommended Dosage Modification for Neurologic Toxicity (Including ICANS)
Adverse Reaction | Severity [Based on National Cancer Institute Common Terminology Criteria for Adverse Events (NCI CTCAE), version 4.03.] , [Based on ASTCT 2019 grading for ICANS.] | Actions
 | Grade 1 | - Continue COLUMVI and monitor neurologic toxicity symptoms. - If ICANS, manage per current practice guidelines.
 | Grade 2 | - Withhold COLUMVI until neurologic toxicity symptoms improve to Grade 1 or baseline. [Consider the type of neurologic toxicity before deciding to withhold COLUMVI.] , [See Dosage and Administration (2.2) on restarting COLUMVI after dose delays.] - Provide supportive therapy, and consider neurologic evaluation. - If ICANS, manage per current practice guidelines.
Neurologic Toxicity (including ICANS) [see Warnings and Precautions (5.2)] | Grade 3 | - Withhold COLUMVI until neurologic toxicity symptoms improve to Grade 1 or baseline for at least 7 days., [Evaluate benefit-risk before restarting COLUMVI.] - For Grade 3 neurologic events lasting more than 7 days, consider permanently discontinuing COLUMVI. - Provide supportive therapy, and consider neurology evaluation. - If ICANS, manage per current practice guidelines.
 | Grade 4 | - Permanently discontinue COLUMVI. - Provide supportive therapy, which may include intensive care, and consider neurology evaluation. - If ICANS, manage per current practice guidelines.

Other Adverse Reactions

Table 6: Recommended Dosage Modifications for Other Adverse Reactions
Adverse Reactions [Based on NCI CTCAE, version 4.03.] | Severity | Actions
Infections [see Warnings and Precautions (5.3)] | Grades 1 – 4 | - Withhold COLUMVI in patients with active infection until the infection resolves. [See Dosage and Administration (2.2) on restarting COLUMVI after dose delays.] - For Grade 4, consider permanent discontinuation of COLUMVI.
 | Grade 1 | - Monitor for signs and symptoms of compression or obstruction due to mass effect secondary to tumor flare.
Tumor flare [see Warnings and Precautions (5.4)] | Grades 2 – 4 | - Monitor for signs and symptoms of compression or obstruction due to mass effect secondary to tumor flare, and institute appropriate treatment including antihistamine and corticosteroids. - Withhold COLUMVI until tumor flare resolves.
Neutropenia | Absolute neutrophil count less than 0.5 × 10^9/L | - Withhold COLUMVI until absolute neutrophil count is 0.5 × 10^9/L or higher.
Thrombocytopenia | Platelet count less than 50 × 10^9/L | - Withhold COLUMVI until platelet count is 50 × 10^9/L or higher.
Other Adverse Reactions [see Adverse Reactions (6.1)] | Grade 3 or higher | - Withhold COLUMVI until the toxicity resolves to Grade 1 or baseline.

2.5 Preparation into an Intravenous Bag

This section describes preparation of all doses of COLUMVI into an intravenous bag. For preparation instructions for the 2.5 mg dose into an intravenous syringe, see subsection 2.6 [see Dosage and Administration (2.6)].

Preparation

- Parenteral drug products should be inspected visually for particulate matter and discoloration prior to administration, whenever solution and container permit. COLUMVI is a colorless clear solution. Discard the vial if the solution is cloudy, discolored, or contains visible particles.
- Use aseptic technique when preparing the COLUMVI diluted solution for intravenous infusion.

Dilution for Intravenous Bag Infusion

- Determine the dose, total volume of COLUMVI solution, and the number of COLUMVI vials needed (see Table 7).
- Select an appropriate size infusion bag of 0.9% Sodium Chloride Injection or 0.45% Sodium Chloride Injection (see Table 7).
  - COLUMVI diluted with 0.9% Sodium Chloride Injection is compatible with intravenous infusion bags composed of polyvinyl chloride (PVC), polyethylene (PE), polypropylene (PP) or polyolefin.
  - COLUMVI diluted with 0.45% Sodium Chloride Injection is compatible with intravenous infusion bags composed of PVC.
- Prepare the infusion bag by withdrawing and discarding the volume from the infusion bag according to Table 7.
- Withdraw the required volume of COLUMVI from the vial(s) using a sterile needle and syringe and dilute into the infusion bag to a final concentration of 0.1 mg/mL to 0.6 mg/mL according to Table 7.

Table 7: Dilution of COLUMVI into an intravenous infusion bag
Dose of COLUMVI | Size of 0.9% Sodium Chloride Injection or 0.45% Sodium Chloride Injection infusion bag | Volume to be withdrawn and discarded from the infusion bag | Volume of COLUMVI to be added to the infusion bag | Total volume to be infused
2.5 mg | 50 mL | 27.5 mL | 2.5 mL | 25 mL
10 mg | 50 mL | 10 mL | 10 mL | 50 mL
10 mg | 100 mL | 10 mL | 10 mL | 100 mL
30 mg | 50 mL | 30 mL | 30 mL | 50 mL
30 mg | 100 mL | 30 mL | 30 mL | 100 mL

- Discard any unused COLUMVI left in the vial.
- Gently invert the infusion bag to mix the solution, in order to avoid excess foaming. Do not shake.

2.6 Preparation of 2.5 mg Dose into an Intravenous Syringe

This section describes the alternative method of preparation of the 2.5 mg dose of COLUMVI into an intravenous syringe. For preparation instructions for all doses into an intravenous infusion bag, see subsection 2.5 [see Dosage and Administration (2.5)].

Preparation

- Parenteral drug products should be inspected visually for particulate matter and discoloration prior to administration, whenever solution and container permit. COLUMVI is a colorless clear solution. Discard the vial if the solution is cloudy, discolored, or contains visible particles.
- Use aseptic technique when preparing the COLUMVI diluted solution for intravenous syringe infusion.

Dilution for Intravenous Syringe Infusion (Alternative Method for 2.5 mg Dose Only)

- Draw 22.5 mL of 0.9% Sodium Chloride Injection or 0.45% Sodium Chloride Injection into a 30 mL syringe composed of PP (see Table 8).
- Withdraw 2.5 mL of COLUMVI from the vial using a sterile needle into a second syringe (see Table 8). Discard any unused COLUMVI left in the vial.
- Attach a connector to the two syringes and transfer COLUMVI into the 30 mL syringe. The final concentration of COLUMVI should be 0.1 mg/mL.

Table 8: Dilution of COLUMVI into an intravenous syringe
Dose of COLUMVI | Volume of 0.9% Sodium Chloride Injection or 0.45% Sodium Chloride Injection to be added to the syringe | Volume of COLUMVI to be added to the syringe | Total volume to be infused
2.5 mg | 22.5 mL | 2.5 mL | 25 mL

- Disconnect the syringes. Draw air into the syringe containing the COLUMVI diluted solution and close.
- Gently invert the syringe to mix the solution, in order to avoid excessive foaming. Do not shake.
- Remove air bubbles from the syringe before administration.

2.7 Storage and Administration

Storage of Diluted Product

Immediately use diluted COLUMVI solution. If not used immediately, the diluted solution can be stored:

- Refrigerated at 2°C to 8°C (36°F to 46°F) for up to 64 hours, or
- At room temperature up to 25°C (77°F) for up to 4 hours.

Do not freeze the diluted infusion solution.

Discard diluted infusion solution if storage time exceeds these limits.

COLUMVI Administration

- Administer COLUMVI as an intravenous infusion only through a dedicated infusion line that includes a sterile 0.2-micron in-line filter using an intravenous infusion pump or syringe pump. Prime the infusion line with the diluted infusion solution.
- No incompatibilities have been observed with infusion sets with product-contacting surfaces of polyurethane (PUR), PVC, PE, polybutadiene (PBD), polyetherurethane (PEU), polycarbonate (PC), silicone, polytetrafluoroethylene (PTFE), or acrylonitrile butadiene styrene (ABS), and in-line filter membranes composed of polyethersulfone (PES) or polysulfone.
- See Table 1 for duration of infusion. The maximum time for the administration of the diluted infusion solution may be extended up to 8 hours (see Table 4).
- To ensure the entire dose of COLUMVI is administered, replace the empty infusion bag or syringe with an infusion bag or syringe containing 0.9% Sodium Chloride Injection or 0.45% Sodium Chloride Injection connected to the same infusion line. Continue the infusion at the same rate until the recommended infusion duration is reached according to Table 1.
- Do not mix COLUMVI with other drugs.

3 DOSAGE FORMS AND STRENGTHS

Injection:

- 2.5 mg/2.5 mL (1 mg/mL) clear, colorless solution in a single-dose vial.
- 10 mg/10 mL (1 mg/mL) clear, colorless solution in a single-dose vial.

4 CONTRAINDICATIONS

None.

5 WARNINGS AND PRECAUTIONS

5.1 Cytokine Release Syndrome

COLUMVI can cause serious and fatal cytokine release syndrome (CRS) [see Adverse Reactions (6.1)].

Among 145 patients who received COLUMVI, CRS occurred in 70%, with Grade 1 CRS developing in 52% of all patients, Grade 2 in 14%, Grade 3 in 2.8%, and Grade 4 in 1.4%. The most common manifestations of CRS included fever, tachycardia, hypotension, chills, and hypoxia.

CRS occurred in 56% of patients after the 2.5 mg dose of COLUMVI, 35% after the 10 mg dose, 29% after the initial 30 mg target dose, and 2.8% after subsequent doses. With the first step-up dose of COLUMVI, the median time to onset of CRS (from the start of infusion) was 14 hours (range: 5 to 74 hours). CRS after any dose resolved in 98% of cases, with a median duration of CRS of 2 days (range: 1 to 14 days). Recurrent CRS occurred in 34% of all patients. CRS can first occur with the 10 mg dose; of 135 patients treated with the 10 mg dose of COLUMVI, 15 patients (11%) experienced their first CRS event with the 10 mg dose, of which 13 events were Grade 1, 1 event was Grade 2, and 1 event was Grade 3.

Administer COLUMVI in a facility equipped to monitor and manage CRS. Initiate therapy according to the COLUMVI step-up dosing schedule to reduce the risk of CRS, administer pretreatment medications, and ensure adequate hydration [Dosage and Administration (2.3)]. Patients should be hospitalized during and for 24 hours after completing infusion of the 2.5 mg step-up dose. Patients who experienced any grade CRS during the 2.5 mg step-up dose should be hospitalized during and for 24 hours after completion of the 10 mg step-up dose. For subsequent doses, patients who experienced Grade ≥ 2 CRS with the previous infusion should be hospitalized during and for 24 hours after the next COLUMVI infusion [see Dosage and Administration (2.1 and 2.2)].

At the first sign of CRS, immediately evaluate patients for hospitalization, manage per current practice guidelines, and administer supportive care; withhold or permanently discontinue COLUMVI based on severity [see Dosage and Administration (2.4)].

5.2 Neurologic Toxicity

COLUMVI can cause serious and fatal neurologic toxicity, including Immune Effector Cell-Associated Neurotoxicity (ICANS) [see Adverse Reactions (6.1)].

Among 145 patients who received COLUMVI, the most frequent neurologic toxicities of any grade were headache (10%), peripheral neuropathy (8%), dizziness or vertigo (7%), and mental status changes (4.8%, including confusional state, cognitive disorder, disorientation, somnolence, and delirium). Grade 3 or higher neurologic adverse reactions occurred in 2.1% of patients and included somnolence, delirium, and myelitis. Cases of ICANS of any grade occurred in 4.8% of patients.

Coadministration of COLUMVI with other products that cause dizziness or mental status changes may increase the risk of neurologic toxicity. Optimize concomitant medications and hydration to avoid dizziness or mental status changes. Institute fall precautions as appropriate.

Monitor patients for signs and symptoms of neurologic toxicity, evaluate, and provide supportive therapy; withhold or permanently discontinue COLUMVI based on severity [see Dosage and Administration (2.4)].

Evaluate patients who experience neurologic toxicity such as tremors, dizziness, or adverse reactions that may impair cognition or consciousness promptly, including potential neurology evaluation. Advise affected patients to refrain from driving and/or engaging in hazardous occupations or activities, such as operating heavy or potentially dangerous machinery, until the neurologic toxicity fully resolves.

5.3 Serious Infections

COLUMVI can cause serious or fatal infections [see Adverse Reactions (6.1)].

Serious infections were reported in 16% of patients, including Grade 3 or 4 infections in 10%, and fatal infections in 4.8% of patients. Grade 3 or higher infections reported in ≥ 2% of patients were COVID-19 infection (6%), including COVID-19 pneumonia, and sepsis (4.1%). Febrile neutropenia occurred in 3.4% of patients.

COLUMVI should not be administered to patients with an active infection. Administer antimicrobial prophylaxis according to guidelines. Monitor patients before and during COLUMVI treatment for infection and treat appropriately. Withhold or consider permanent discontinuation of COLUMVI based on severity [see Dosage and Administration (2.4)].

5.4 Tumor Flare

COLUMVI can cause serious tumor flare [see Adverse Reactions (6.1)]. Manifestations include localized pain and swelling at the sites of the lymphoma lesions and/or dyspnea from new pleural effusions.

Tumor flare was reported in 12% of patients who received COLUMVI, including Grade 2 tumor flare in 4.8% of patients and Grade 3 tumor flare in 2.8%. Recurrent tumor flare occurred in two (12%) of the affected patients. Most tumor flare events occurred during Cycle 1, with a median time to first onset of 2 days (range: 1 to 16 days) after the first dose of COLUMVI. The median duration was 3.5 days (range: 1 to 35 days).

Patients with bulky tumors or disease located in close proximity to airways or a vital organ should be monitored closely during initial therapy. Monitor for signs and symptoms of compression or obstruction due to mass effect secondary to tumor flare, and institute appropriate treatment. Withhold COLUMVI until tumor flare resolves [see Dosage and Administration (2.4)].

5.5 Embryo-Fetal Toxicity

Based on its mechanism of action, COLUMVI may cause fetal harm when administered to a pregnant woman. Advise pregnant women of the potential risk to the fetus. Advise females of reproductive potential to use effective contraception during treatment with COLUMVI and for 1 month after the last dose [see Use in Specific Populations (8.1, 8.3)].

6 ADVERSE REACTIONS

The following clinically significant adverse reactions are described elsewhere in the labeling:

- Cytokine Release Syndrome [see Warnings and Precautions (5.1)]
- Neurologic Toxicity [see Warnings and Precautions (5.2)]
- Serious Infections [see Warnings and Precautions (5.3)]
- Tumor Flare [see Warnings and Precautions (5.4)]

6.1 Clinical Trials Experience

Because clinical trials are conducted under widely varying conditions, adverse reaction rates observed in the clinical trials of a drug cannot be directly compared to rates in the clinical trials of another drug and may not reflect the rates observed in practice.

Relapsed or Refractory DLBCL, NOS or LBCL Arising from Follicular Lymphoma

Study NP30179

The safety of COLUMVI was evaluated in Study NP30179, a multi-cohort, multicenter, single-arm clinical trial that included 154 adult patients with relapsed or refractory large B-cell lymphoma (LBCL) after two or more lines of systemic therapy [see Clinical Studies (14.1)]. The trial required an ECOG performance status of 0 or 1, absolute neutrophil count ≥ 1,500/µL, platelet count ≥ 75,000/µL independent of transfusion, serum creatinine ≤ 1.5 × upper limit of normal (ULN) or creatinine clearance (CLcr) ≥ 50 mL/min, and hepatic transaminases ≤ 3 × ULN. The trial excluded patients with active or previous central nervous system (CNS) lymphoma or CNS disease, acute infection, recent infection requiring intravenous antibiotics, or prior allogeneic hematopoietic stem cell transplantation (HSCT).

Patients received pretreatment with a single dose of obinutuzumab on Day 1 of Cycle 1 (seven days prior to start of COLUMVI). Following premedication, COLUMVI was administered by intravenous infusion according to the step-up dosing schedule with 2.5 mg on Day 8 of Cycle 1, and 10 mg on Day 15 of Cycle 1. Patients received the 30 mg COLUMVI dose by intravenous infusion on Day 1 of subsequent cycles for a maximum of 12 cycles (including step-up dosing). Each cycle was 21 days. Patients were hospitalized during and for 24 hours following completion of at least the first step-up dose.

Of the 154 patients who initiated study treatment, 145 received COLUMVI; nine patients (6%) did not receive COLUMVI due to infection, progressive disease, or patient decision. Patients received a median of 5 cycles of COLUMVI with 30% receiving all 12 cycles of COLUMVI.

Of patients who received COLUMVI, the median age was 66 years (range: 21 to 90 years); 66% were male; 77% were White, 4.8% were Asian, 1.4% were Black or African American, 6% were Hispanic or Latino. The main diagnoses were DLBCL, NOS and LBCL arising from follicular lymphoma.

Serious adverse reactions occurred in 48% of patients who received COLUMVI. Serious adverse reactions in ≥ 2% of patients included CRS, COVID-19 infection, sepsis, and tumor flare. Fatal adverse reactions occurred in 5% of patients from COVID-19 infection (3.4%), sepsis (1.4%), and delirium (0.6%).

Adverse reactions led to permanent discontinuation of COLUMVI in 7% of patients, including from infection, delirium, neutropenia, and CRS. Adverse reactions led to dose interruptions of COLUMVI in 19% of patients, most frequently (≥ 2%) from neutropenia and thrombocytopenia.

The most common (≥ 20%) adverse reactions, excluding laboratory terms, were CRS, musculoskeletal pain, rash, and fatigue. The most common Grade 3 to 4 laboratory abnormalities (≥ 20%) were lymphocyte count decreased, phosphate decreased, neutrophil count decreased, uric acid increased, and fibrinogen decreased.

Table 9 summarizes adverse reactions observed in Study NP30179.

Table 9: Select Adverse Reactions (≥ 10%) in Patients with Relapsed or Refractory LBCL Who Received COLUMVI in Study NP30179
Adverse Reactions | COLUMVI N=145
Adverse Reactions | All grades (%) | Grade 3 or 4 (%)
Immune system disorders
Cytokine release syndrome | 70 | 4.1
Musculoskeletal and connective tissue disorders
Musculoskeletal pain [Includes musculoskeletal pain, back pain, bone pain, flank pain, myalgia, neck pain, and pain in extremity.] | 21 | 2.1
General disorders
Fatigue [Includes fatigue and asthenia.] | 20 | 1.4
Pyrexia | 16 | 0
Edema [Includes edema, edema peripheral, swelling face, and face edema.] | 10 | 0
Skin and subcutaneous tissue disorders
Rash [Includes rash, rash pruritic, rash maculo-papular, dermatitis, dermatitis acneiform, dermatitis exfoliative, erythema, palmar erythema, pruritus, and rash erythematous.] | 20 | 1.4
Gastrointestinal disorders
Constipation | 14 | 0
Diarrhea | 14 | 0
Nausea | 10 | 0
Abdominal pain [Includes abdominal pain, abdominal discomfort, and abdominal pain upper.] | 10 | 0
Neoplasms
Tumor flare | 12 | 2.8
Neurologic Disorders
Headache | 10 | 0
The table includes a combination of grouped and ungrouped terms. Adverse reactions were graded using NCI CTCAE version 4.03, with the exception of CRS, which was graded per ASTCT consensus criteria in most cases.

Clinically relevant adverse reactions occurring in < 10% of patients who received COLUMVI included infusion-related reaction, peripheral neuropathy, pneumonia, mental status changes, vomiting, tumor lysis syndrome, febrile neutropenia, upper respiratory tract infection, sepsis, herpes zoster infection, gastrointestinal hemorrhage, tremor, myelitis, and colitis.

Table 10 summarizes laboratory abnormalities in Study NP30179.

Table 10: Select Laboratory Abnormalities (≥ 20%) That Worsened from Baseline in Patients with Relapsed or Refractory LBCL Who Received COLUMVI in Study NP30179
Laboratory Abnormality | COLUMVI [The denominator used to calculate the rate varied from 137 to 145 based on the number of patients with a baseline value and at least one post-treatment value.]
Laboratory Abnormality | All Grades (%) | Grade 3 or 4 (%)
Hematology
Lymphocytes decreased | 90 | 83
Hemoglobin decreased | 72 | 8
Neutrophils decreased | 56 | 26 [Grade 4 neutrophil decrease occurred in 9% of patients.]
Platelets decreased | 56 | 8
Chemistry
Fibrinogen decreased | 84 | 21
Phosphate decreased | 69 | 28
Sodium decreased | 49 | 7
Calcium decreased | 48 | 2.1
Gamma-glutamyl transferase increased | 33 | 9
Potassium decreased | 32 | 6
Uric acid increased | 23 | 23

7 DRUG INTERACTIONS

For certain CYP substrates where minimal concentration changes may lead to serious adverse reactions, monitor for toxicities or drug concentrations of such CYP substrates when coadministered with COLUMVI.

Glofitamab-gxbm causes the release of cytokines [see Clinical Pharmacology (12.2)] that may suppress the activity of CYP enzymes, resulting in increased exposure of CYP substrates. Increased exposure of CYP substrates is more likely to occur after the first dose of COLUMVI on Cycle 1 Day 8 and up to 14 days after the first 30 mg dose on Cycle 2 Day 1 and during and after CRS [see Warnings and Precautions (5.1)].

8 USE IN SPECIFIC POPULATIONS

8.1 Pregnancy

Risk Summary

Based on its mechanism of action COLUMVI may cause fetal harm when administered to a pregnant woman [see Clinical Pharmacology (12.1)]. There are no available data on the use of COLUMVI in pregnant women to evaluate for a drug-associated risk. No animal reproductive and developmental toxicity studies have been conducted with glofitamab-gxbm.

Glofitamab-gxbm causes T-cell activation and cytokine release; immune activation may compromise pregnancy maintenance. In addition, based on expression of CD20 on B cells and the finding of B-cell depletion in non-pregnant animals, glofitamab-gxbm can cause B-cell lymphocytopenia in infants exposed to glofitamab-gxbm in-utero. Human immunoglobulin G (IgG) is known to cross the placenta; therefore, COLUMVI has the potential to be transmitted from the mother to the developing fetus. Advise women of the potential risk to the fetus.

In the U.S. general population, the estimated background risk of major birth defects and miscarriage in clinically recognized pregnancies is 2% to 4% and 15% to 20%, respectively.

8.2 Lactation

Risk Summary

There are no data on the presence of glofitamab-gxbm in human milk or the effects on the breastfed child or milk production. Because human IgG is present in human milk, and there is potential for glofitamab-gxbm absorption leading to B-cell depletion, advise women not to breastfeed during treatment with COLUMVI and for 1 month after the last dose of COLUMVI.

8.3 Females and Males of Reproductive Potential

COLUMVI may cause fetal harm when administered to a pregnant woman [see Use in Specific Populations (8.1)].

Pregnancy Testing

Verify pregnancy status in females of reproductive potential prior to initiating COLUMVI.

Contraception

Females

Advise female patients of reproductive potential to use effective contraception during treatment with COLUMVI and for 1 month after the last dose of COLUMVI [see Use in Specific Populations (8.1)].

8.4 Pediatric Use

The safety and efficacy of COLUMVI in pediatric patients have not been established.

8.5 Geriatric Use

Of the 145 patients with relapsed or refractory LBCL who received COLUMVI in study NP30179, 55% were 65 years of age or older, and 23% were 75 years of age or older. There was a higher rate of fatal adverse reactions, primarily from COVID-19, in patients 65 years of age or older compared to younger patients [see Adverse Reactions (6.1)]. No overall differences in efficacy were observed between patients 65 years of age or older and younger patients.

11 DESCRIPTION

Glofitamab-gxbm is a bispecific CD20-directed CD3 T-cell engager. It is a recombinant humanized anti-CD20 anti-CD3ɛ bispecific immunoglobulin G1 (IgG1) monoclonal antibody produced in Chinese hamster ovary (CHO) cells. Glofitamab-gxbm has an approximate molecular weight of 197 kDa.

COLUMVI (glofitamab-gxbm) injection is a sterile, preservative-free, colorless, clear solution supplied in single-dose vials for intravenous infusion.

COLUMVI is supplied in 2.5 mg/2.5 mL and 10 mg/10 mL single-dose vials at a concentration of 1 mg/mL. Each mL of solution contains 1 mg glofitamab-gxbm, histidine (0.63 mg), histidine hydrochloride monohydrate (3.34 mg), methionine (1.49 mg), polysorbate 20 (0.5 mg), sucrose (82.15 mg), and Water for Injection, USP, at pH 5.5.

12 CLINICAL PHARMACOLOGY

12.1 Mechanism of Action

Glofitamab-gxbm is a bispecific antibody that binds to CD20 expressed on the surface of B cells, and to CD3 receptor expressed on the surface of T cells. Glofitamab-gxbm causes T-cell activation and proliferation, secretion of cytokines, and the lysis of CD20-expressing B cells. Glofitamab-gxbm showed anti-tumor activity in vivo in mouse models of DLBCL.

12.2 Pharmacodynamics

Circulating B Cell Count

Peripheral B cell counts decreased to undetectable levels (< 5 cells/microliter) in 86.5% of patients by Cycle 1 Day 7 after obinutuzumab pretreatment of 1,000 mg on Cycle 1 Day 1, and in 88.2% of patients by Cycle 1 Day 10 after the first glofitamab-gxbm dose of 2.5 mg on Cycle 1 Day 8.

Cytokine Concentrations

Plasma concentrations of cytokines (IL-2, IL-6, IL-10, TNF-α, and IFN-γ) were measured and transient elevation of cytokines was observed at doses of 0.045 mg and above. After administration of the recommended dosage of COLUMVI, the highest elevation of cytokines was generally observed within 6 hours after the first glofitamab-gxbm dose of 2.5 mg on Cycle 1 Day 8. The elevated cytokine levels generally returned to baseline within 48 hours after the first 30 mg dose on Cycle 2 Day 1.

12.3 Pharmacokinetics

The pharmacokinetics of glofitamab-gxbm was determined following pretreatment with a single dose of obinutuzumab of 1,000 mg and the pharmacokinetic parameters are presented as geometric mean (CV%) unless otherwise specified. Glofitamab-gxbm exposure increased dose-proportionally over the dose range from 0.005 to 30 mg (0.000167 to 1 time the recommended treatment dosage). Glofitamab-gxbm exposure parameters are summarized in Table 11 for the approved recommended dosage of COLUMVI.

Table 11: Exposure Parameters of Glofitamab-gxbm Following Pretreatment with a Single Dose of Obinutuzumab of 1,000 mg
 | AUCtau (day∙mcg/mL) | Cmax (mcg/mL) | Ctrough (mcg/mL)
First full 30 mg dose | 44.5 (55%) | 9.41 (27%) | 0.52 (83%)
Steady state [Steady state values are approximated at Cycle 6 (week 18).] 30 mg dose | 48.6 (33%) | 9.44 (26%) | 0.59 (67%)
Data presented as geometric mean (CV%). AUCtau = area under the concentration-time curve over one 21-day cycle; Cmax = maximum glofitamab-gxbm concentration; Ctrough = glofitamab-gxbm concentration prior to next dose; CV = geometric coefficient of variation.

Distribution

The glofitamab-gxbm total volume of distribution is 5.6 L (24%).

Elimination

At steady state, the glofitamab-gxbm terminal half-life is 7.6 days (24%) and the clearance is 0.617 L/day (33%).

Metabolism

Glofitamab-gxbm is expected to be metabolized into small peptides by catabolic pathways.

Specific Populations

No clinically significant changes in the pharmacokinetics of glofitamab-gxbm were observed based on age (21 to 90 years), body weight (31 to 148 kg), sex, mild to moderate renal impairment (CLcr 30 to < 90 mL/min as estimated by Cockcroft-Gault formula) and mild hepatic impairment (total bilirubin > ULN to ≤ 1.5 × ULN or AST > ULN).

The effects of severe renal impairment (CLcr 15 to < 30 mL/min), end-stage renal disease (CLcr < 15 mL/min), or moderate to severe hepatic impairment (total bilirubin > 1.5 × ULN and any AST), and race/ethnicity on the pharmacokinetics of glofitamab-gxbm are unknown.

Drug Interaction Studies

No clinical studies evaluating the drug interaction potential of glofitamab-gxbm have been conducted.

12.6 Immunogenicity

The observed incidence of antidrug antibodies (ADA) is highly dependent on the sensitivity and specificity of the assay. Differences in assay methods preclude meaningful comparisons of the incidence of ADA in the study described below with the incidence of ADA in other studies, including those of glofitamab-gxbm.

During treatment in Study NP30179 (up to 9 months) [see Clinical Studies (14.1)], using an enzyme-linked immunosorbent assay (ELISA), the incidence of anti-glofitamab antibody formation was 1.1% (5/448) in patients treated with COLUMVI. Because of the low occurrence of ADAs, the effect of these antibodies on the pharmacokinetics, pharmacodynamics, safety, and/or effectiveness of glofitamab-gxbm is unknown.

13 NONCLINICAL TOXICOLOGY

13.1 Carcinogenesis, Mutagenesis, Impairment of Fertility

No carcinogenicity or genotoxicity studies have been conducted with glofitamab-gxbm.

Fertility studies have not been conducted with glofitamab-gxbm.

14 CLINICAL STUDIES

14.1 Relapsed or Refractory DLBCL, NOS or LBCL Arising from Follicular Lymphoma

The efficacy of COLUMVI was evaluated in Study NP30179 (NCT03075696), an open-label, multicenter, multicohort, single-arm clinical trial that included patients with relapsed or refractory LBCL after two or more lines of systemic therapy. The trial required an ECOG performance status of 0 or 1, absolute neutrophil count ≥ 1,500/µL, platelet count ≥ 75,000/µL independent of transfusion, serum creatinine ≤ 1.5 × ULN or CLcr ≥ 50 mL/min, and hepatic transaminases ≤ 3 × ULN. The trial excluded patients with active or previous CNS lymphoma or CNS disease, acute infection, recent infection requiring intravenous antibiotics, or prior allogeneic HSCT.

Following pretreatment with obinutuzumab on Cycle 1 Day 1, patients received COLUMVI by intravenous infusion, starting with a 2.5 mg step-up dose on Cycle 1 Day 8, followed by a 10 mg step-up dose on Cycle 1 Day 15, then 30 mg on Cycle 2 Day 1 and on Day 1 of each subsequent cycle. The cycle length was 21 days. COLUMVI was administered for up to 12 cycles unless patients experienced progressive disease or unacceptable toxicity.

The efficacy population consists of 132 patients with de novo DLBCL, NOS (80%) or LBCL arising from follicular lymphoma (20%) who received at least one dose of COLUMVI. The median age was 67 years (range: 21 to 90 years), 64% were male, 77% were White, 4.5% were Asian, 0.8% were Black or African American, 5% were Hispanic or Latino. The median number of prior lines of systemic therapy was 3 (range: 2 to 7). Most patients (83%) had refractory disease to the last therapy, 55% had primary refractory disease, 30% had received CAR-T cell therapy, and 19% had received autologous HSCT.

Efficacy was based on objective response rate (ORR) and duration of response (DOR), as determined by an Independent Review Committee (IRC) using the 2014 Lugano criteria.

Efficacy results are summarized in Table 12. The median time to first response was 42 days (range: 31 to 178 days). Among responders, the estimated median follow-up for DOR was 11.6 months.

Table 12: IRC-Assessed Efficacy in Patients with Relapsed or Refractory DLBCL, NOS or LBCL Arising from Follicular Lymphoma
Outcome per IRC | COLUMVI N=132
Overall Response Rate, n (%) | 74 (56)
(95% CI) | (47, 65)
Complete Response, n (%) | 57 (43)
(95% CI) | (35, 52)
Partial Response, n (%) | 17 (13)
(95% CI) | (8, 20)
Duration of Response [From date of first response (PR or CR) until disease progression or death due to any cause.] | N = 74
Median DOR, months (95% CI) [Kaplan-Meier estimate.] | 18.4 (11.4, NE)
9-month estimate, % (95% CI) | 68.5 (56.7, 80.3)
CI = confidence interval; NE = not estimable

16 HOW SUPPLIED/STORAGE AND HANDLING

COLUMVI (glofitamab-gxbm) injection is a sterile, preservative-free, colorless, clear solution for intravenous infusion.

COLUMVI is supplied as:

Carton Contents | NDC
One 2.5 mg/2.5 mL (1 mg/mL) single-dose vial | NDC 50242-125-01
One 10 mg/10 mL (1 mg/mL) single-dose vial | NDC 50242-127-01

STORAGE AND HANDLING

Store refrigerated at 2°C to 8°C (36°F to 46°F) in original carton to protect from light. Do not freeze. Do not shake.

17 PATIENT COUNSELING INFORMATION

Advise the patient to read the FDA-approved patient labeling (Medication Guide).

Cytokine Release Syndrome

Inform patients of the risk of CRS. Advise patients to seek immediate medical attention if they experience signs and symptoms of CRS (fever, hypoxia, hypotension, chills and tachycardia) [see Warnings and Precautions (5.1)].

Provide patients with the Patient Wallet Card that they should carry with them at all times. This card describes symptoms of CRS which, if experienced, should prompt the patient to seek immediate medical attention.

Neurologic Toxicity

Discuss the signs and symptoms associated with neurologic toxicity, including ICANS, headache, peripheral neuropathy, dizziness, or mental status changes. Advise patients to immediately contact their healthcare provider if they experience any signs or symptoms of neurologic toxicity. Advise patients who experience neurologic toxicity that impairs consciousness to refrain from driving or operating heavy or potentially dangerous machinery until neurologic toxicity resolves [see Warnings and Precautions (5.2)].

Serious Infections

Advise patients that COLUMVI can cause serious infections. Advise patients to notify their healthcare provider immediately if they develop any signs of infection (e.g., fever, chills, weakness) [see Warnings and Precautions (5.3)].

Tumor Flare

Inform patients of the potential risk of tumor flare reaction and to report any signs and symptoms associated with this event (e.g., localized pain and swelling) to their healthcare provider for evaluation [see Warnings and Precautions (5.4)].

Embryo-Fetal Toxicity

Advise pregnant women of the potential risk to a fetus. Advise females of reproductive potential to inform their healthcare provider if they are pregnant or become pregnant. Advise females of reproductive potential to use effective contraception during treatment with COLUMVI and for 1 month after the last dose [see Warnings and Precautions (5.5) and Use in Specific Populations (8.1, 8.3)].

Advise women not to breastfeed while receiving treatment with COLUMVI and for 1 month after the last dose [see Use in Specific Populations (8.2)].

COLUMVI® [glofitamab-gxbm]

Manufactured by:
Genentech, Inc.
A Member of the Roche Group
1 DNA Way
South San Francisco, CA 94080-4990

U.S. License No.: 1048

COLUMVI® is a registered trademark of Genentech, Inc.

©2025 Genentech, Inc. All rights reserved.

MEDICATION GUIDE
COLUMVI® (ko-loom-vee)
(glofitamab-gxbm)
injection, for intravenous infusion

What is the most important information I should know about COLUMVI?

COLUMVI can cause Cytokine Release Syndrome (CRS), a serious side effect that is common during treatment with COLUMVI, and can also be serious and lead to death.

- Call your healthcare provider or get emergency medical help right away if you develop any signs or symptoms of CRS, including:

- fever of 100.4°F (38°C) or higher
- chills or shaking
- fast or irregular heartbeat

- dizziness or light-headedness
- trouble breathing
- shortness of breath

- Due to the risk of CRS, you will receive COLUMVI on a "step-up dosing schedule".
  - A single dose of a medicine called obinutuzumab will be given to you on the first day of your first treatment cycle (Day 1 of Cycle 1).
  - You will start the COLUMVI step-up dosing schedule a week after the obinutuzumab dose. The step-up dosing schedule is when you receive smaller "step-up" doses of COLUMVI on Day 8 and Day 15 of Cycle 1. This is to help reduce your risk of CRS. You should be hospitalized during your infusion and for 24 hours after receiving the first step-up dose on Day 8. You should be hospitalized during your infusion and for 24 hours after receiving the second step-up dose on Day 15 if you experienced CRS during the first step-up dose.
  - You will receive your first full dose of COLUMVI a week after the second step-up dose (this will be Day 1 of Cycle 2).
  - If your dose of COLUMVI is delayed for any reason, you may need to repeat the "step-up dosing schedule".
  - If you had more than mild CRS with your previous dose of COLUMVI, you should be hospitalized during and for 24 hours after receiving your next dose of COLUMVI.
  - Before each dose of COLUMVI, you will receive medicines to help reduce your risk of CRS and infusion-related reactions.
  - See "How will I receive COLUMVI?" for more information about how you will receive COLUMVI.
- Your healthcare provider will monitor you for CRS during treatment with COLUMVI and may treat you in a hospital if you develop signs and symptoms of CRS. Your healthcare provider may temporarily stop or completely stop your treatment with COLUMVI if you have severe side effects.
- Carry the COLUMVI Patient Wallet Card with you at all times and show it to all of your healthcare providers. The COLUMVI Patient Wallet Card lists the signs and symptoms of CRS you should get emergency medical help for right away.

See "What are the possible side effects of COLUMVI?" for more information about side effects.

What is COLUMVI?
COLUMVI is a prescription medicine used to treat adults with certain types of diffuse large B-cell lymphoma (DLBCL) or large B-cell lymphoma (LBCL) that has come back (relapsed) or that did not respond to previous treatment (refractory), and who have received 2 or more prior treatments for their cancer.
It is not known if COLUMVI is safe and effective in children.

Before receiving COLUMVI, tell your healthcare provider about all of your medical conditions, including if you:

- have an infection
- have kidney problems
- are pregnant or plan to become pregnant. COLUMVI may harm your unborn baby.
  Females who are able to become pregnant:
  - Your healthcare provider should do a pregnancy test before you start treatment with COLUMVI.
  - You should use effective birth control (contraception) during treatment and for 1 month after your last dose of COLUMVI. Talk to your healthcare provider about what birth control method is right for you during this time.
  - Tell your healthcare provider right away if you become pregnant or think you may be pregnant during treatment with COLUMVI.
- are breastfeeding or plan to breastfeed. It is not known if COLUMVI passes into your breastmilk. Do not breastfeed during treatment and for 1 month after your last dose of COLUMVI.

Tell your healthcare provider about all the medicines you take, including prescription and over-the-counter medicines, vitamins, and herbal supplements.

How will I receive COLUMVI?

- COLUMVI will be given to you by your healthcare provider by infusion through a needle placed in your vein (intravenous infusion).
- Your COLUMVI treatment schedule is divided into cycles that are 21 days (3 weeks) long.
- On Day 1 of Cycle 1, your healthcare provider will give you a single dose of a medicine called obinutuzumab by intravenous infusion. You will then receive COLUMVI on Day 8 and Day 15 of Cycle 1. Starting with Cycle 2, you will receive COLUMVI 1 time every three weeks.

Your healthcare provider will decide how many treatment cycles you will receive of COLUMVI. See "What is the most important information I should know about COLUMVI?" for more information about how you will receive COLUMVI.

What should I avoid while receiving COLUMVI?
Do not drive, operate heavy machinery, or do other dangerous activities if you develop dizziness, confusion, shaking (tremors), sleepiness, or any other symptoms that impair consciousness until your signs and symptoms go away. These may be signs and symptoms of neurologic problems.
See "What are the possible side effects of COLUMVI?" for more information about signs and symptoms of neurologic problems.

What are the possible side effects of COLUMVI?

COLUMVI may cause serious side effects, including:

- Cytokine Release Syndrome. See "What is the most important information I should know about COLUMVI?"
- Neurologic problems. COLUMVI can cause serious neurologic problems that may lead to death. Your healthcare provider will monitor you for neurologic problems during treatment with COLUMVI. Your healthcare provider may also refer you to a healthcare provider who specializes in neurologic problems. Tell your healthcare provider right away if you develop any signs or symptoms of neurologic problems, including:

- headache
- confusion and disorientation
- difficulty paying attention or understanding things
- trouble speaking
- sleepiness

- memory problems
- numbness, tingling, or weakness of the hands or feet
- dizziness
- shaking (tremors)

- Serious infections. COLUMVI can cause serious infections that may lead to death. Your healthcare provider will monitor you for signs and symptoms of infection and treat you as needed. Tell your healthcare provider right away if you develop any signs of infection, including: fever, chills, weakness, cough, shortness of breath, or sore throat.
- Growth in your tumor or worsening of tumor related problems (tumor flare). Tell your healthcare provider if you get any of these signs or symptoms of tumor flare:
  - tender or swollen lymph nodes
  - pain or swelling at the site of the tumor
  - chest pain
  - cough
  - trouble breathing

Your healthcare provider may temporarily stop or completely stop treatment with COLUMVI if you develop certain side effects.
The most common side effects of COLUMVI include: CRS, muscle and bone pain, rash, and tiredness.
The most common severe abnormal lab test results with COLUMVI include: decreased white blood cells, decreased phosphate (an electrolyte), increased uric acid levels, and decreased fibrinogen (a protein that helps with blood clotting).
These are not all the possible side effects of COLUMVI.
Call your doctor for medical advice about side effects. You may report side effects to FDA at 1-800-FDA-1088.

General information about the safe and effective use of COLUMVI.
Medicines are sometimes prescribed for purposes other than those listed in a Medication Guide. You can ask your healthcare provider or pharmacist for information about COLUMVI that is written for health professionals.

What are the ingredients in COLUMVI?
Active ingredient: glofitamab-gxbm
Inactive ingredients: histidine, histidine hydrochloride monohydrate, methionine, polysorbate 20, sucrose, and Water for injection.
Manufactured by: Genentech, Inc., A Member of the Roche Group, 1 DNA Way, South San Francisco, CA 94080-4990
U.S. License No.: 1048
For more information, go to www.COLUMVI.com or call 1-877-436-3683.

This Medication Guide has been approved by the U.S. Food and Drug Administration.

Revised: 6/2025

PRINCIPAL DISPLAY PANEL - 10 mg/10 mL Vial Carton

NDC 50242-127-01

Columvi®

(glofitamab-gxbm)
Injection

10 mg/10 mL
(1 mg/mL)

For Intravenous Infusion
After Dilution.

Single-Dose Vial.
Discard Unused Portion.

ATTENTION: Dispense the enclosed
Medication Guide to each patient.

1 vial

Rx only
Genentech

11038205

PRINCIPAL DISPLAY PANEL - 2.5 mg/2.5 mL Vial Carton

NDC 50242-125-01

Columvi®

(glofitamab-gxbm)
Injection

2.5 mg/2.5 mL
(1 mg/mL)

For Intravenous Infusion
After Dilution.

Single-Dose Vial.
Discard Unused Portion.

ATTENTION: Dispense the enclosed
Medication Guide to each patient.

1 vial

Rx only
Genentech

11038250